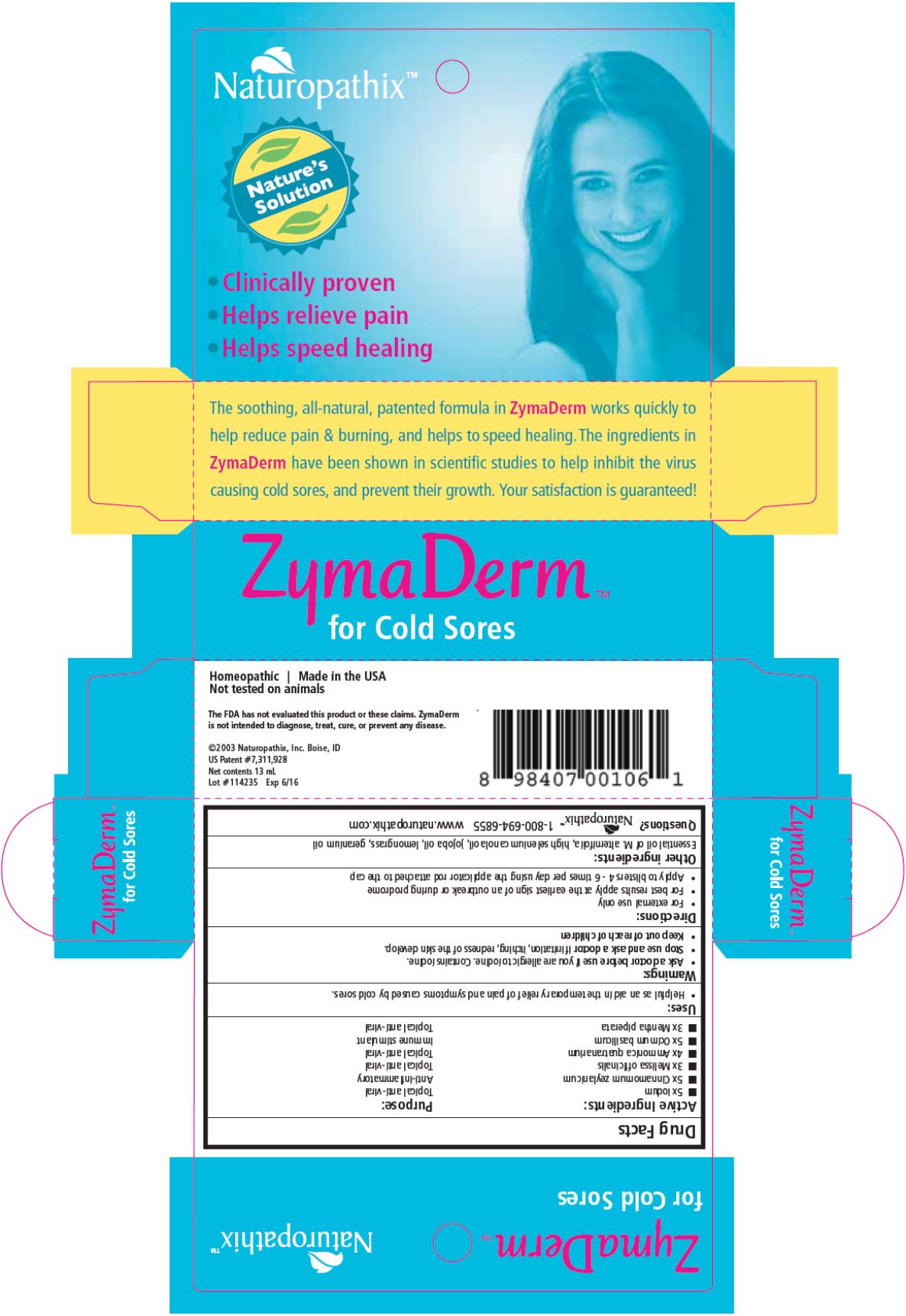 DRUG LABEL: ZymaDerm for Cold Sores
NDC: 69163-4132 | Form: LIQUID
Manufacturer: Naturopathix, Inc.
Category: homeopathic | Type: HUMAN OTC DRUG LABEL
Date: 20210115

ACTIVE INGREDIENTS: IODINE 5 [hp_X]/13 mL; CINNAMOMUM CAMPHORA WHOLE 5 [hp_X]/13 mL; MELISSA OFFICINALIS 3 [hp_X]/13 mL; BETA VULGARIS 4 [hp_X]/13 mL; BASIL 5 [hp_X]/13 mL; MENTHA PIPERITA 3 [hp_X]/13 mL
INACTIVE INGREDIENTS: TEA TREE OIL; JOJOBA OIL; CANOLA OIL

ZymaDerm for Cold Sores

Drug Facts

Active Ingredient

5x Iodum

Purpose

Topical anti-viral

Active Ingredient

5x Cinnamomum camphora

Purpose

Anti-inflammatory

Active Ingredient

3x Melissa officinalis

Purpose

Topical anti-viral

Active Ingredient

4x Ammonica quatranarium

Purpose

Topical anti-viral

Active Ingredient

5x Ocimum basilicum

Purpose

Immune stimulant

Active Ingredient

3x Mentha piperata

Purpose

Topical anti-viral

Uses:

Helpful as an aid in the relief of skin symptoms caused by cold sores.

Directions:

Apply to blisters and sores every 2 hours or at least 4 times a day. Begin application at the earliest sign of prodromal symptoms such as itching, tingling, burning, or pain. Minimize contact with normal skin.

KEEP OUT OF REACH OF CHILDREN.

NOT TO BE TAKEN INTERNALLY. CONTAINS IODINE.

Discontinue if redness of surrounding skin develops, or if pain or discomfort develop. If there is any development you are unsure about, stop ZymaDerm™ and call 1-800-694-6855 to discuss your concerns. IF YOU ARE ALLERGIC TO IODINE CONSULT YOUR PHYSICIAN PRIOR TO USE. If swallowed, give water. Flush with water if accidental contact with eyes occurs. Spills may be cleaned with rubbing alcohol.

Other Ingredients:

M. alternifolia, Jojoba oil, high selenium canola oil

Distributed by Naturopathix, Inc. Boise, ID 1-800-694-6855
Net Contents ½ fl. oz.
©2003 Naturopathix, Inc. Boise, ID All rights reserved. Homeopathic
US Patent # 7,311,928

Principal Display Panel

ZymaDerm TM
for Cold Sores